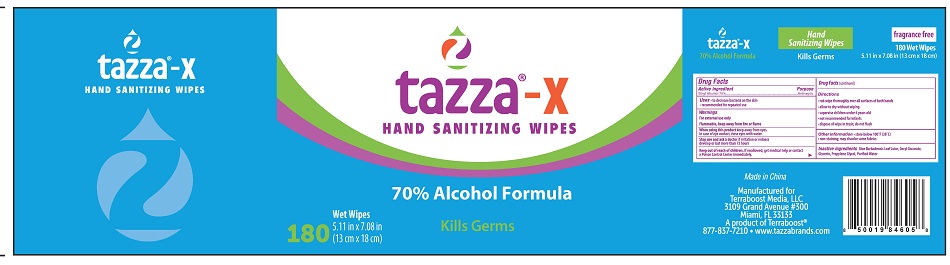 DRUG LABEL: Tazza-X Hand Sanitizing Wipes
NDC: 76370-0008 | Form: CLOTH
Manufacturer: Tazza Brands East Inc.
Category: otc | Type: HUMAN OTC DRUG LABEL
Date: 20240124

ACTIVE INGREDIENTS: ALCOHOL 70 mL/100 mL
INACTIVE INGREDIENTS: WATER; GLYCERIN; ALOE VERA LEAF; PROPYLENE GLYCOL; DECYL GLUCOSIDE

Tazza Hand Sanitizing Wipes Alcohol Formula

Drug Facts

Active ingredient

Ethyl Alcohol 70%

Purpose

Antiseptic

Uses

- to decrease bacteria on the skin
- recommended for repeated use

Warnings

For external use only

Flammable. Keep away from fire or flame.

When using this product keep away from eyes. In case of eye contact, rinse eyes with water.

Stop use and ask a doctor if irritation or redness develop or last more than 72 hours

Keep out of reach of children. If swallowed, get medical help or contact a Poison Control Center right away.

Directions

- rub wipe thoroughly over all surfaces of both hands
- allow to dry without wiping
- supervise children under 6 years old
- not recommended for infants
- dispose of wipe in trash; do not flush

Other information

- store below 100°F (38°C)
- non-staining; may discolor some fabrics

INACTIVE INGREDIENT

Inactive ingredients Aloe Barbadensis Leaf Juice, Decyl Glucoside, Glycerin, Propylene Glycol, Purified Water

Made in China

Manufactured for Terraboost Media, LLC

3109 Grand Avenue #300

Miami, FL 33133

A product of Terraboost®

877-837-7210 • www.tazzabrands.com

PACKAGE LABEL

tazza-X

HAND SANITIZING WIPES

70% alcohol formula

Kills Germs

180 Wet Wipes

5.11 in. x 7.08 in. (13cm x 18 cm)